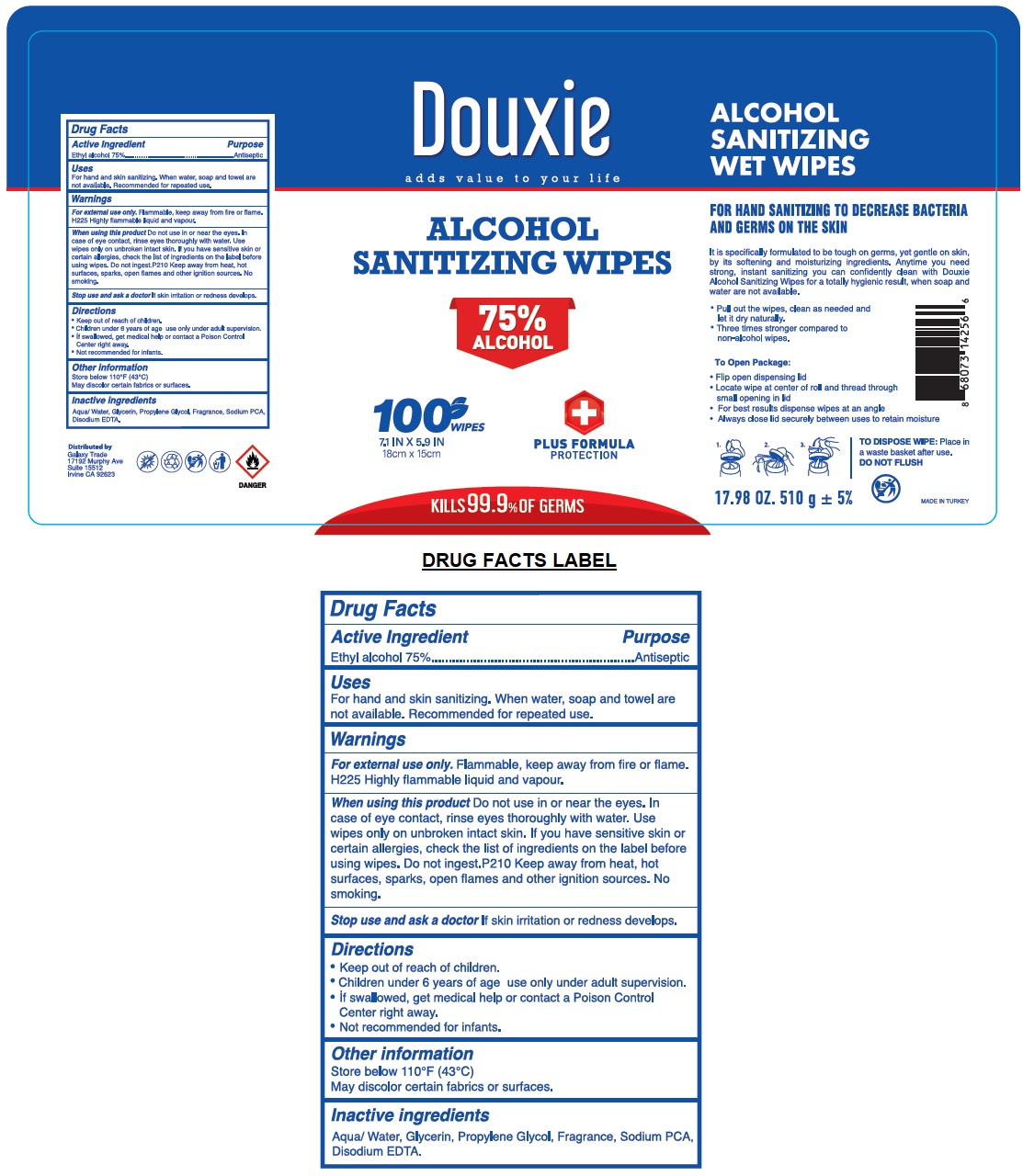 DRUG LABEL: Douxie ALCOHOL SANITIZING WIPES
NDC: 78089-051 | Form: CLOTH
Manufacturer: Endeks Kimya Sanayi Ve Ticaret Anonim Sirketi
Category: otc | Type: HUMAN OTC DRUG LABEL
Date: 20201230

ACTIVE INGREDIENTS: ALCOHOL 75 mL/100 mL
INACTIVE INGREDIENTS: WATER; GLYCERIN; PROPYLENE GLYCOL; SODIUM PYRROLIDONE CARBOXYLATE; EDETATE DISODIUM ANHYDROUS

Douxie ALCOHOL SANITIZING WIPES

Active Ingredient

Ethyl alcohol 75%

Purpose

Antiseptic

Uses

For hand and skin sanitizing. When water, soap and towel are not available. Recommended for repeated use.

Warnings

For external use only. Flammable, keep away from fire or flame. H225 Highly flammable liquid and vapour.

When using this product Do not use in or near the eyes. In case of eye contact, rinse eyes thoroughly with water. Use wipes only on unbroken intact skin. If you have sensitive skin or certain allergies, check the list of ingredients on the label before using wipes. Do not ingest. P210 Keep away from heat, hot surfaces, sparks, open flames and other ignition sources. No smoking.

Stop use and ask a doctor If skin irritation or redness develops.

• Keep out of reach of children.

• Children under 6 years of age use only under adult supervision.

• If swallowed, get medical help or contact a Poison Control Center right away.

• Not recommended for infants.

Directions

• Pull out the wipes, clean as need and let it dry naturally.

• Three times stronger compared to non-alcohol wipes.

To Open Package:

• Flip open dispensing lid

• Locate wipe at center of roll and thread through small opening in lid

• For best results dispense wipes at an angle

• Always close lid securely between uses to retain moisture

TO DISPOSE WIPE: Place in a waste basket after use.

DO NOT FLUSH

Other information

Store below 110°F (43°C)

May discolor certain fabrics or surfaces.

Inactive ingredients

Aqua/ Water, Glycerin, Propylene Glycol, Fragrance, sodium PCA, Disodium EDTA.

adds value to your life

75% ALCOHOL

+ PLUS FORMULA PROTECTION

KILLS 99.9% OF GERMS
FOR HAND SANITIZING TO DECREASE BACTERIA AND GERMS ON THE SKIN

It is specifically formulated to be tough on germs, yet gentle on skin, by its softening and moisturizing ingredients. Anytime you need strong, instant sanitizing you can confidently clean with Douxie Alcohol Sanitizing Wipes for a totally hygienic result, when soap and water are not available.
Distributed by
Galaxy Trade
17192 Murphy Ave
Suite 15512
Irvine CA 92623

MADE IN TURKEY